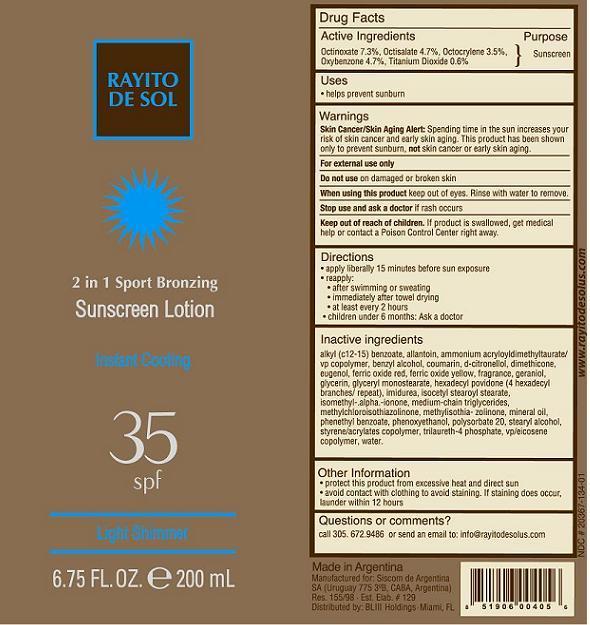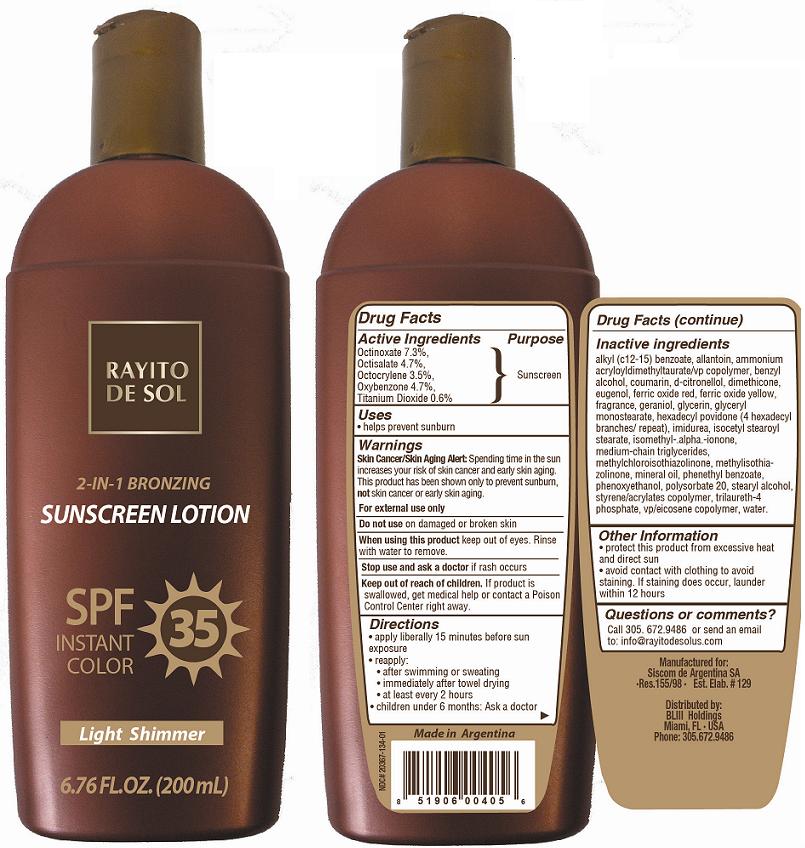 DRUG LABEL: Rayito de Sol
NDC: 20367-134 | Form: CREAM
Manufacturer: Siscom de Argentina S.A.
Category: otc | Type: HUMAN OTC DRUG LABEL
Date: 20130111

ACTIVE INGREDIENTS: OCTINOXATE 15.04 g/200 mL; OCTISALATE 9.68 g/200 mL; OXYBENZONE 9.68 g/200 mL; OCTOCRYLENE 7.21 g/200 mL; TITANIUM DIOXIDE 1.24 g/200 mL
INACTIVE INGREDIENTS: ALKYL (C12-15) BENZOATE; ALLANTOIN; AMMONIUM ACRYLOYLDIMETHYLTAURATE/VP COPOLYMER; BENZYL ALCOHOL; COUMARIN; .BETA.-CITRONELLOL, (R)-; DIMETHICONE; EUGENOL; FERRIC OXIDE RED; FERRIC OXIDE YELLOW; GERANIOL; GLYCERIN; GLYCERYL MONOSTEARATE; HEXADECYL POVIDONE (4 HEXADECYL BRANCHES/REPEAT); IMIDUREA; ISOCETYL STEAROYL STEARATE; ISOMETHYL-.ALPHA.-IONONE; MEDIUM-CHAIN TRIGLYCERIDES; METHYLCHLOROISOTHIAZOLINONE; METHYLISOTHIAZOLINONE; MINERAL OIL; PHENETHYL BENZOATE; PHENOXYETHANOL; POLYSORBATE 20; STEARYL ALCOHOL; TRILAURETH-4 PHOSPHATE; Water; BUTYL ACRYLATE; N-VINYLPYRROLIDINONE

Drug Facts

Active Ingredients

Octinoxate 7.3%
Octisalate 4.7%
Octocrylene 3.5%
Oxybenzone 4.7%
Titanium Dioxide 0.6%

Purpose

Sunscreen

Uses

• helps prevent sunburn

Warnings

Skin Cancer/Skin Aging Alert: Spending time in the sun increases your risk of skin cancer and early skin aging. This product has been shown only to prevent sunburn, not skin cancer or early skin aging.
For external use only
Do not use on damaged or broken skin

When using this product

keep out of eyes. Rinse with water to remove.

Stop use and ask a doctor

if rash occurs

Keep out of the reach of children

If product is swallowed, get medical help or contact a Poison Control Center right away.

Directions

• apply liberally 15 minutes before sun exposure
• reapply:
• after swimming or sweating
• immediately after towel drying
• at least every 2 hours
• children under 6 months: Ask a doctor

Inactive Ingredients

alkyl (c12-15) benzoate, allantoin, ammonium acryloyldimethyltaurate/vp copolymer, benzyl alcohol, coumarin, d-citronellol, dimethicone, eugenol, ferric oxide red, ferric oxide yellow, fragrance, geraniol, glycerin, glyceryl monostearate, hexadecyl povidone (4 hexadecyl branches/ repeat), imidurea, isocetyl stearoyl stearate, isomethyl-.alpha.-ionone, medium-chain triglycerides, methylchloroisothiazolinone, methylisothia- zolinone, mineral oil, phenethyl benzoate, phenoxyethanol, polysorbate 20, stearyl alcohol, styrene/acrylates copolymer, trilaureth-4 phosphate, vp/eicosene copolymer, water.

Other Information

• protect this product from excessive heat and direct sun
• avoid contact with clothing to avoid staining. If staining does occur, launder within 12 hours

Questions or Comments?

Call 305. 672.9486 or send an email to: info@rayitodesolus.com

PACKAGE LABEL

Rayito de Sol® ·
2 in1 Sport Bronzing
Sunscreen Lotion
SPF 35
Light Shimmer
200 mL · 6.76 FL. OZ.